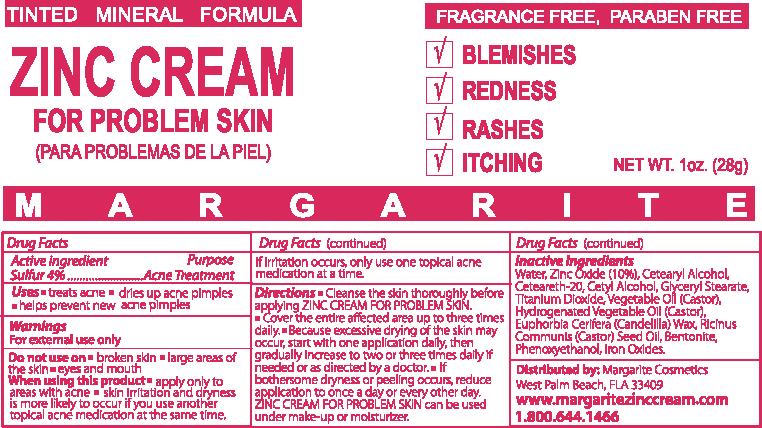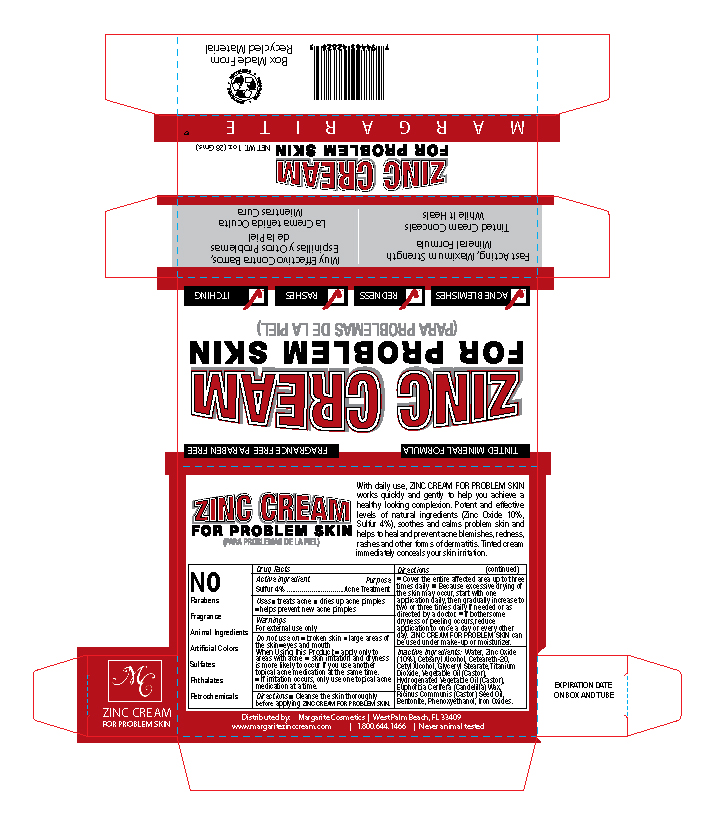 DRUG LABEL: Margarite Zinc Cream
NDC: 76348-413 | Form: CREAM
Manufacturer: Renu Laboratories, LLC
Category: otc | Type: HUMAN OTC DRUG LABEL
Date: 20250610

ACTIVE INGREDIENTS: SULFUR 1.12 g/28 g
INACTIVE INGREDIENTS: WATER 20.7 g/28 g; TITANIUM DIOXIDE; FERROUS OXIDE; CETOSTEARYL ALCOHOL; BENTONITE; PHENOXYETHANOL; CASTOR OIL; CANDELILLA WAX; ZINC OXIDE; POLYOXYL 20 CETOSTEARYL ETHER; HYDROGENATED CASTOR OIL; GLYCERYL MONOSTEARATE; CETYL ALCOHOL

MARGARITE ZINC CREAM

Active ingredient

Sulfur 4%

Do not use on

- broken skin
- large areas of the skin
- eyes and mouth

Purpose

Acne Treatment

QUESTIONS

1.800.644.1466

STOP USE

If excessive skin irritation develops or increases, discontinue use and consult a doctor.

When Using this Product

- apply only to areas with acne
- skin irritation and dryness is more likely to occur if you use another topical acne medication at the same time.
- If irritation occurs, only use one topical acne medication at a time.

Warnings

For external use only

- Keep out of the reach of children.

Inactive Ingredients:

Water, Zinc Oxide (10%), Cetearyl Alcohol, Cetearyl Alcohol, Ceteareth-20, Cetyl Alcohol, Glyceryl Stearate, Titanium Dioxide, Vegetable Oil (Castor), Hydrogenated Vegetable Oil (Castor), Euphorbia Cerifera (Candelilla) Wax, Ricinus Communis (Castor) Seed Oil, Bentonite, Phenoxyethanol, Iron Oxides.

Directions

- Cleanse the skin thoroughly before applying ZINC CREAM FOR PROBLEM SKIN.
- Cover the entire affected area up to three times daily
- Because excessive drying of the skin may occur, start with one application daily, then gradually increase to two or three times daily if needed or as directed by a doctor.
- If bothersome dryness or peeling occurs, reduce application to once a day or every other day. ZINC CREAM FOR PROBLEM SKIN can be used under make-up or moisturizer.

Uses

- treats acne
- dries up acne pimples
- helps prevent new acne pimples

PACKAGE LABEL

TUBE ART FOR MARGARITE ZINC CREAM

Margarite BOX